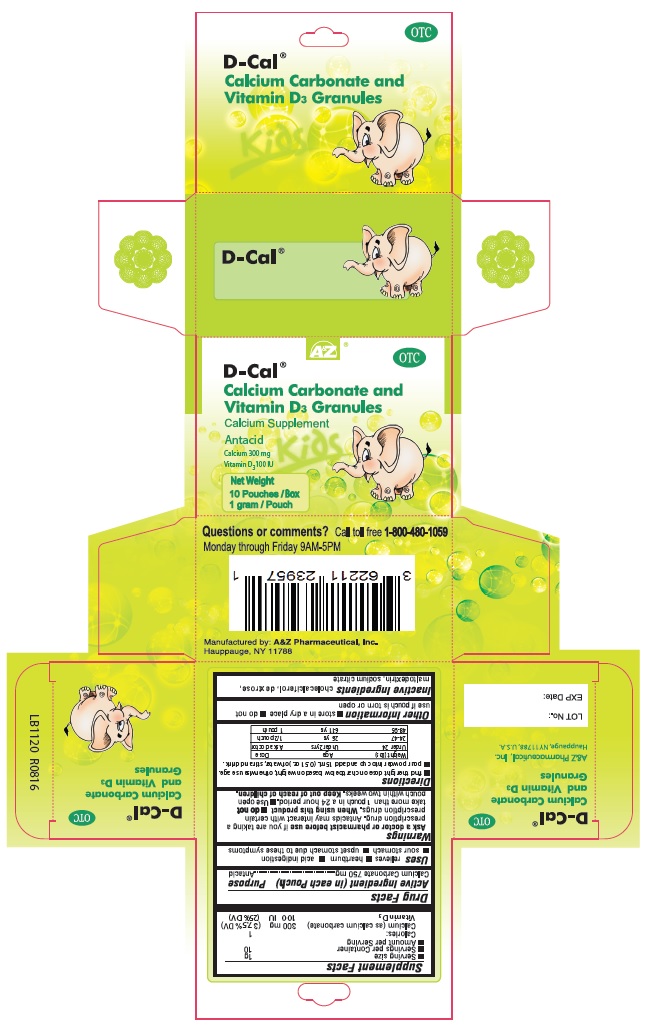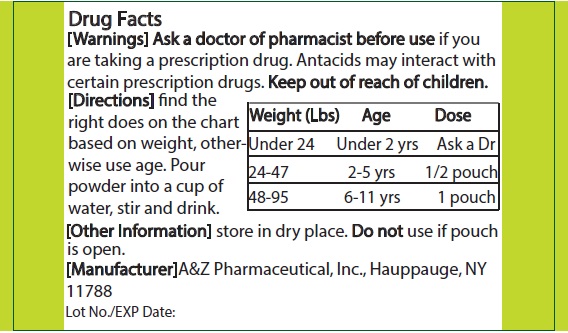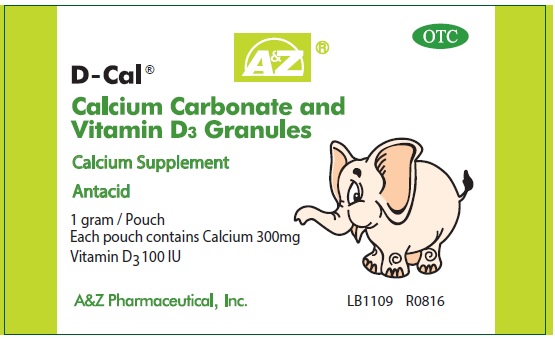 DRUG LABEL: D-Cal Kids
NDC: 62211-239 | Form: GRANULE
Manufacturer: A&Z Pharmaceutical, Inc.
Category: otc | Type: HUMAN OTC DRUG LABEL
Date: 20191003

ACTIVE INGREDIENTS: CALCIUM CARBONATE 750 mg/1 g
INACTIVE INGREDIENTS: CHOLECALCIFEROL; DEXTROSE; MALTODEXTRIN; SODIUM CITRATE

Drug Facts

Active ingredient

Calcium Carbonate 750 mg (in each pouch)

Purpose

Antacid

Uses

Relieves:

- Heartburn
- Acid indigestion
- Sour stomach
- Upset stomach due to these symptoms

Warnings

Ask a doctor or pharmacist before use if you are taking a prescription drug. Antacids may interact with certain prescription drugs.

When using this product:

- do not take more than 1 pouch in a 24 hour period.
- use open pouch within two weeks.

Directions

- Find the right dose on chart below based on weight, otherwise use age.
- Pour powder into cup and add 15mg (0.51 oz.) of water, stir and drink.

Dosing Chart

Weight (lbs) | Age | Dose
Under 24 | Under 2 yrs | Ask a doctor
24-47 | 2-5 yrs | 1/2 pouch
48-95 | 6-11 yrs | 1 pouch

Inactive ingredients

Cholecalciferol, dextrose, maltodextrin, sodium citrate

Other Information

Store in a dry place.

Do not use if pouch is open or torn.

Mfg by: A&Z Pharmaceutical, Inc.

Hauppauge, NY 11788

QUESTIONS

Call toll free 1-800-480-1059 Monday through Friday 9AM-5PM

Principal Display Panel - Carton Label

D-Cal® Kids Granules

Calcium Supplement

Antacid

10 pouches